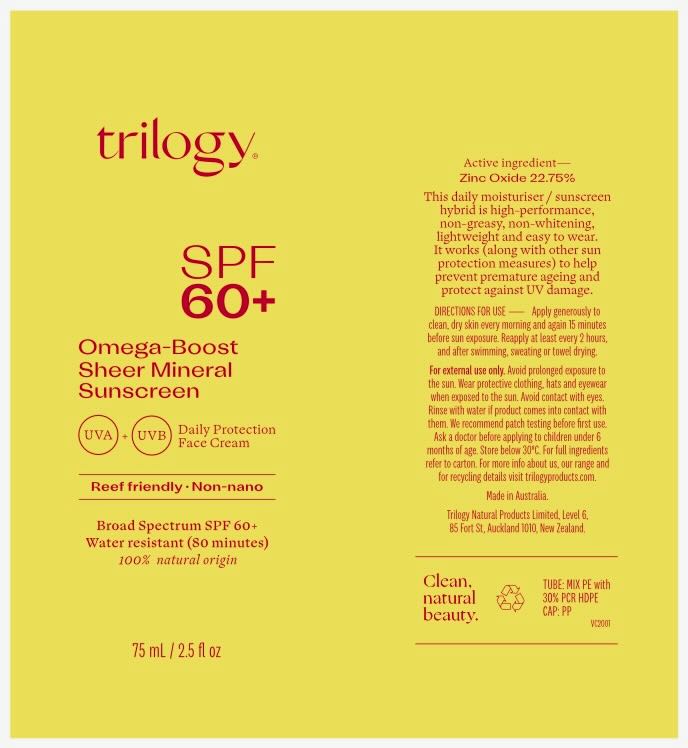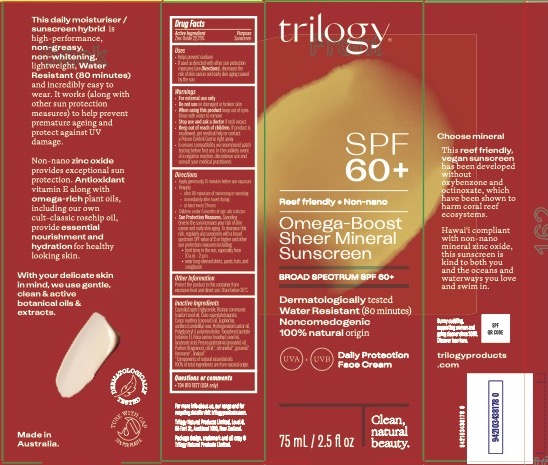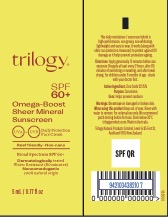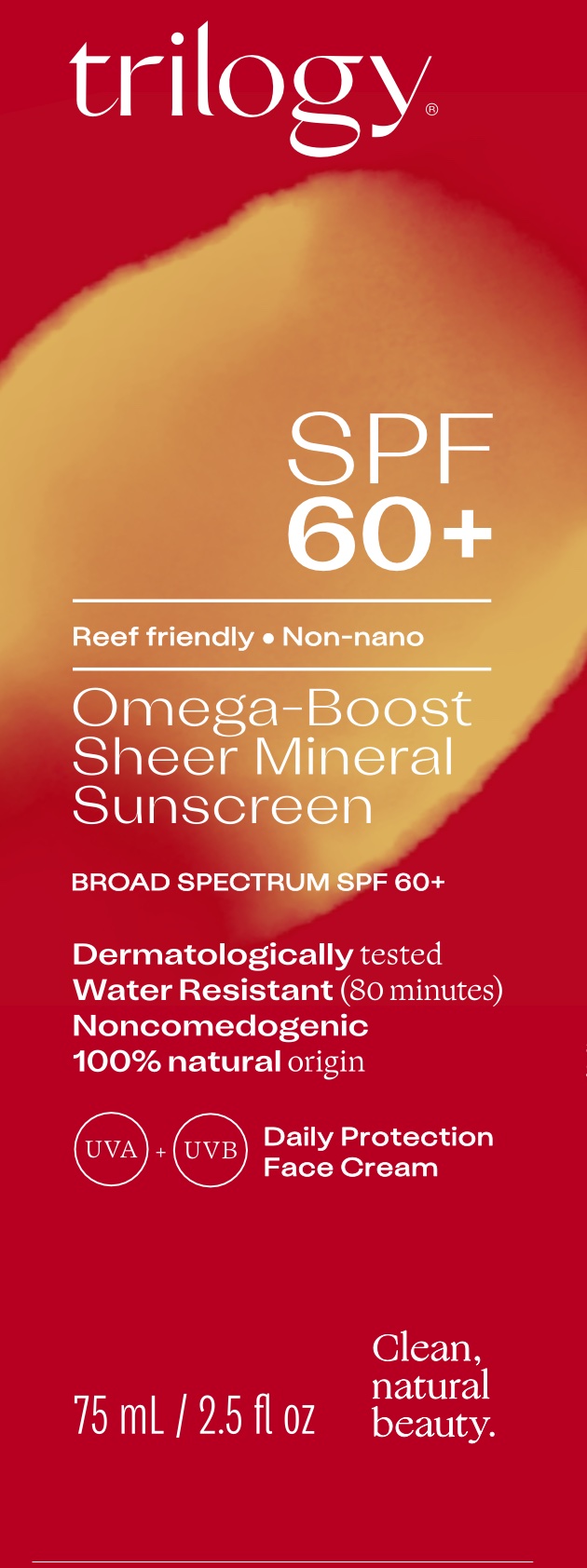 DRUG LABEL: Omega-Boost Sheer Mineral Sunscreen
NDC: 83105-2001 | Form: LOTION
Manufacturer: Trilogy Natural Products Limited
Category: otc | Type: HUMAN OTC DRUG LABEL
Date: 20251203

ACTIVE INGREDIENTS: ZINC OXIDE 229.25 mg/1 mL
INACTIVE INGREDIENTS: ISOSTEARIC ACID; CASTOR OIL; CANDELILLA WAX; HYDROGENATED CASTOR OIL; ROSA MOSCHATA OIL; AVOCADO OIL; COCO-CAPRYLATE/CAPRATE; MEDIUM-CHAIN TRIGLYCERIDES; .ALPHA.-TOCOPHEROL ACETATE; COCONUT OIL; POLYGLYCERYL-3 PENTARICINOLEATE

Trilogy Omega-Boost Sheer Mineral Sunscreen

Active Ingredient

Active Ingredient: Zinc Oxide

Uses

- Helps prevent sunburn
- If used as directed with other sun protection measures (see Directions) decreases risk of skin cancer and early skin aging caused by the sun

Warnings

- For external use only.
- Do not use on damaged or broken skin
- When using this product [bullet] keep out of eyes. Rinse with water to remove.
- Stop use and ask a doctor if [bullet] rash or irritation develops and lasts.
- Keep out of reach of children, If product is swallowed, get medical help or contact poison control centre right away.
- To ensure compatibility, we recommend patch testing before first use. In the unlikely event of a negative reaction, discontinue use and consult your medical practitioner.

Do not use on damaged or broken skin

When using this product

keep out of eyes. Rinse with water to remove.

Keep out of reach of children. If product is swallowed, get medical help or contact Poison Control Center right away.

Directions

- Apply generously 15 minutes before sun exposure”
- Reapply [bullet] after 80 minutes of swimming or sweating [bullet] immediately after towel drying [bullet] at least every 2 hours
- Children under 6 months of age: Ask a doctor
- Sun Protection Measures. Spending time in the sun increases your risk of skin cancer and early skin aging. To decrease this risk, regularly use a sunscreen with a Broad Spectrum SPF value of 15 or higher and other sun protection measures including:  limit time in the sun, especially from 10 a.m. - 2 p.m.  wear long-sleeved shirts, pants, hats, and sunglasses

Inactive ingredients

Coco-caprylate/caprate, polyglyceryl-3 polyricinoleate, Isostearic acid, Castor oil, Caprilic/capric triglyceride, Coconut oil, Candellila wax, Hydrogenated castor oil, Tocopherol acetate, Rosehip oil, Avocado oil, Fragrance

Other Information

Protect the product in this container from excessive heat and direct sun. Store below 30 degrees celcius.

Uses

Helps prevent sunburn.

Trilogy SPF 60+ Omega-Boost Sheer Mineral Sunscreen

NDC 83105-2001-0

Secondary pacakaging

NDC 83105-2001-1

75 mL / 2.5 fl oz

Principal Display Panel:

Inner Container Label

NDC 83105-2001-1

75 mL

Primary Container Label

Sample Size Package

83105-2001-2

5 mL